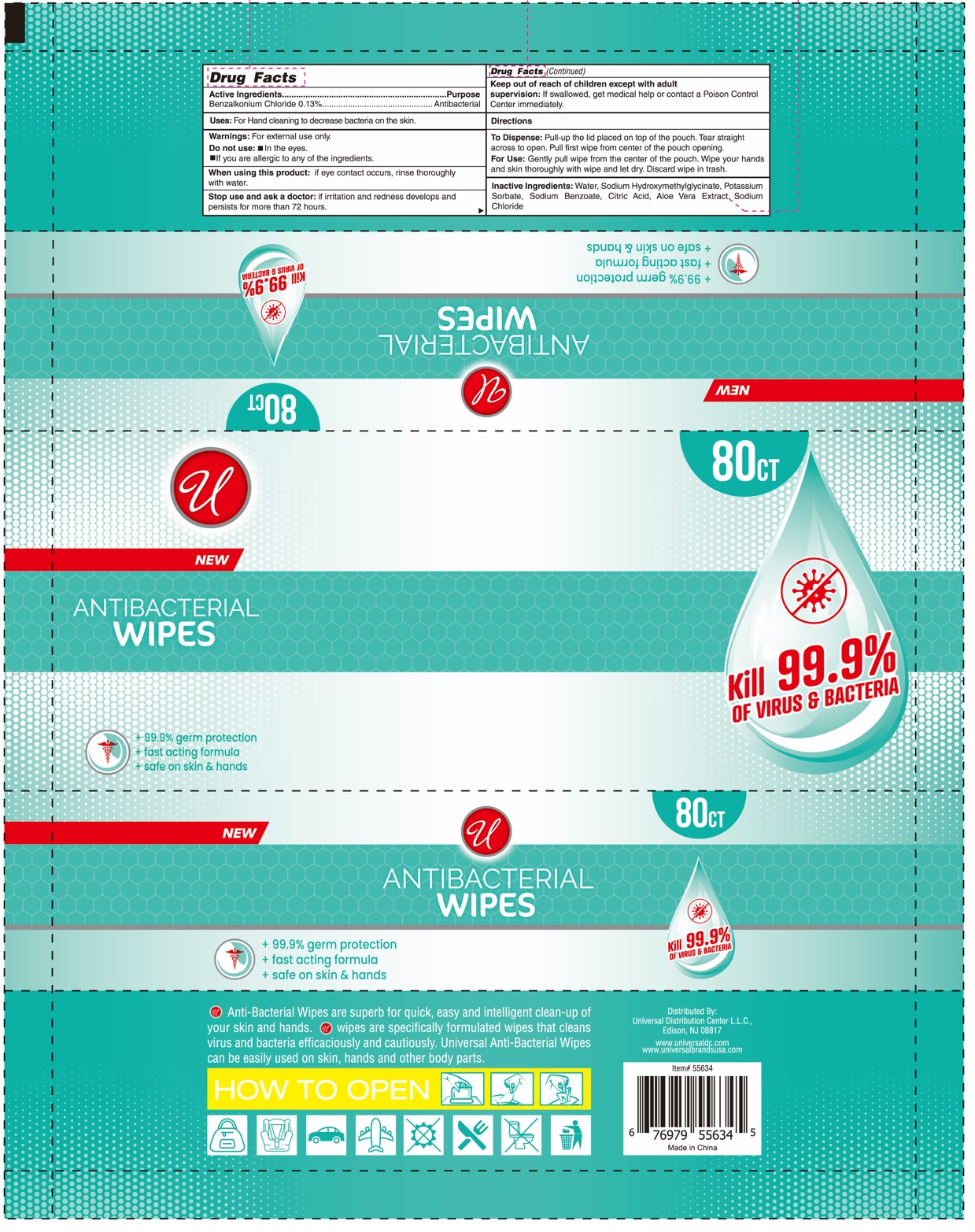 DRUG LABEL: ANTIBACTERIAL WIPES
NDC: 52000-419 | Form: CLOTH
Manufacturer: Universal Distribution Center LLC
Category: otc | Type: HUMAN OTC DRUG LABEL
Date: 20240913

ACTIVE INGREDIENTS: BENZALKONIUM CHLORIDE 0.13 g/100 g
INACTIVE INGREDIENTS: WATER; SODIUM HYDROXYMETHYLGLYCINATE; POTASSIUM SORBATE; SODIUM BENZOATE; CITRIC ACID MONOHYDRATE; ALOE VERA LEAF; SODIUM CHLORIDE

ANTIBACTERIAL WIPES

Active Ingredients

Benzalkonium Chloride 0.13%

Purpose

Antibacterial

Uses:

For Hand cleaning to decrease bacteria on the skin.

Warnings:

For external use only.

Do not use: • in the eyes.
• If you are allergic to any of the ingredients.

When using this product: if eye contact occurs, rinse thoroughly with water.

Stop use and ask a doctor: if irritation and redness develops and persists for more than 72 hours.

Keep out of reach of children except with adult supervision: If swallowed, get medical help or contact a Poison Control Center immediately.

Directions

To Dispense: Pull-up the lid placed on top of the pouch. Tear straight across to open. Pull first wipe from center of the pouch opening.

For Use: Gently pull wipe from the center of the pouch. Wipe your hands and skin thoroughly with wipe and let dry. Discard wipe in trash.

Inactive Ingredients:

Water, Sodium Hydroxymethylglycinate, Potassium Sorbate, Sodium Benzoate, Citric Acid, Aloe Vera Extract, Sodium Chloride

NEW

+ 99.9% germ protection

+ fast acting formula

+ safe on skin & hands

Kill 99.9% OF VIRUS & BACTERIA

Anti-Bacterial Wipes are superb for quick, easy and intelligent clean-up of your skin and hands. wipes are specifically formulated wipes that cleans virus and bacteria efficaciously and cautiously. Universal Anti-Bacterial Wipes can be easily used on the skin, hands and other body parts.

Distributed By:
Universal Distribution Center L.L.C.,
Edison, NJ 08817

www.universaldc.com
www.universalbrandsusa.com

Made in China